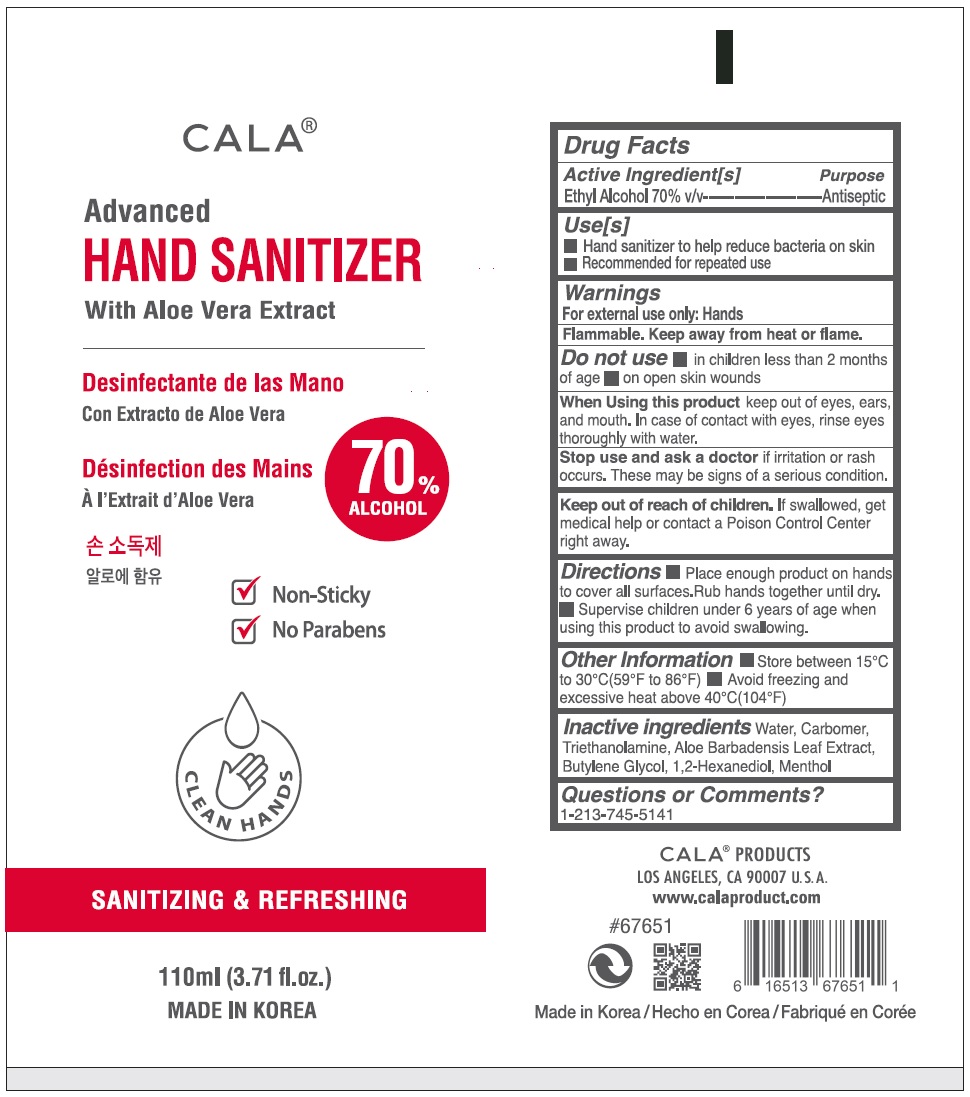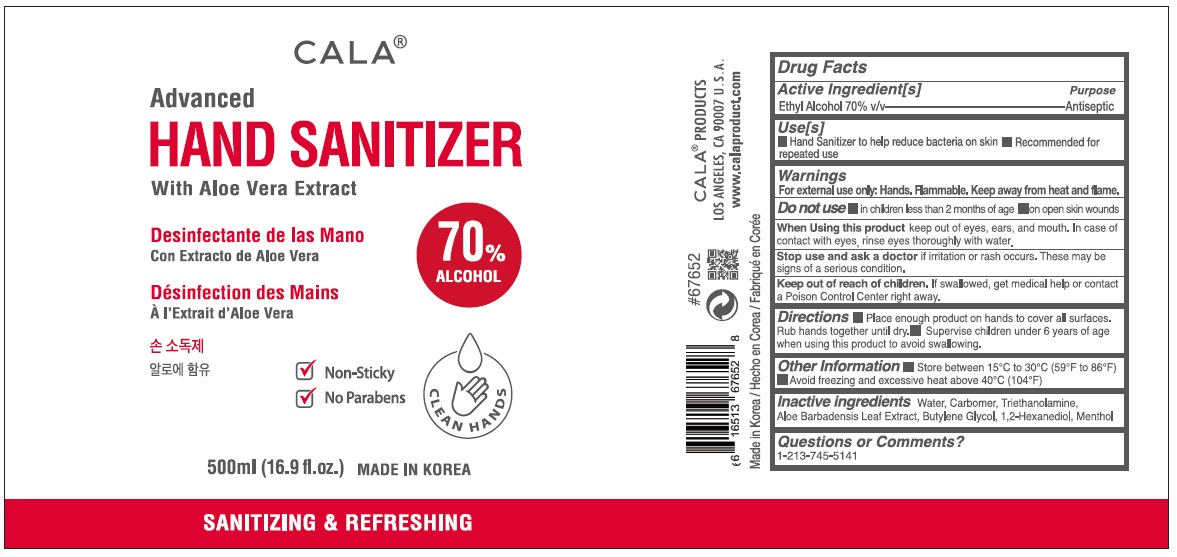 DRUG LABEL: CALA ADVANCED HAND SANITIZER
NDC: 74985-676 | Form: GEL
Manufacturer: Shin's Trading Co., Inc. Dba Cala Products
Category: otc | Type: HUMAN OTC DRUG LABEL
Date: 20200928

ACTIVE INGREDIENTS: ALCOHOL 70 mL/100 mL
INACTIVE INGREDIENTS: WATER; CARBOMER HOMOPOLYMER, UNSPECIFIED TYPE; TROLAMINE; ALOE VERA LEAF; BUTYLENE GLYCOL; 1,2-HEXANEDIOL; MENTHOL, UNSPECIFIED FORM

CALA® Advanced HAND SANITIZER Moisturizing with Aloe Vera Extract

Active Ingredient [s]

Ethyl Alcohol 70% v/v

Purpose

Antiseptic

Use[s]

• Hand sanitizer to help reduce bacteria on the skin

• Recommended for repeated use.

Warnings

For external use only: Hands

Flammable. Keep away from heat or flame.

Do not use • in children less than 2 months of age • on open skin wounds

When Using this product keep out of eyes, ears and mouth. In case of contact with eyes, rinse eyes thoroughly with water.

Stop use and ask a doctor if irritation or rash occurs. These may be signs of a serious condition.

Keep out of reach of children. If swallowed, get medical help or contact a Poison Control Center right away.

DOSAGE AND ADMINISTRATION

Directions • Place enough product on hands to cover all surfaces. Rub hands together until dry. • Supervise children under 6 years of age when using this product to avoid swallowing.

Other Information • Store between 15°C to 30°C(59°F to 86°F) • Avoid freezing and excessive heat above 40°C(104°F)

INACTIVE INGREDIENT

Inactive ingredients Water, Carbomer, Triethanolamine, Aloe Barbadensis Leaf Extract, Butylene Glycol, 1,2-Hexanediol, Menthol

Questions or Comments?

1-213-745-5141

√ Non-Sticky

√ No Parabens

SANITIZING & REFRESHING

MADE IN KOREA

CALA® PRODUCTS

LOS ANGELES, CA 90007, U.S.A.

www.calaproduct.com